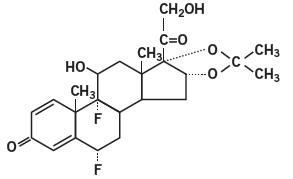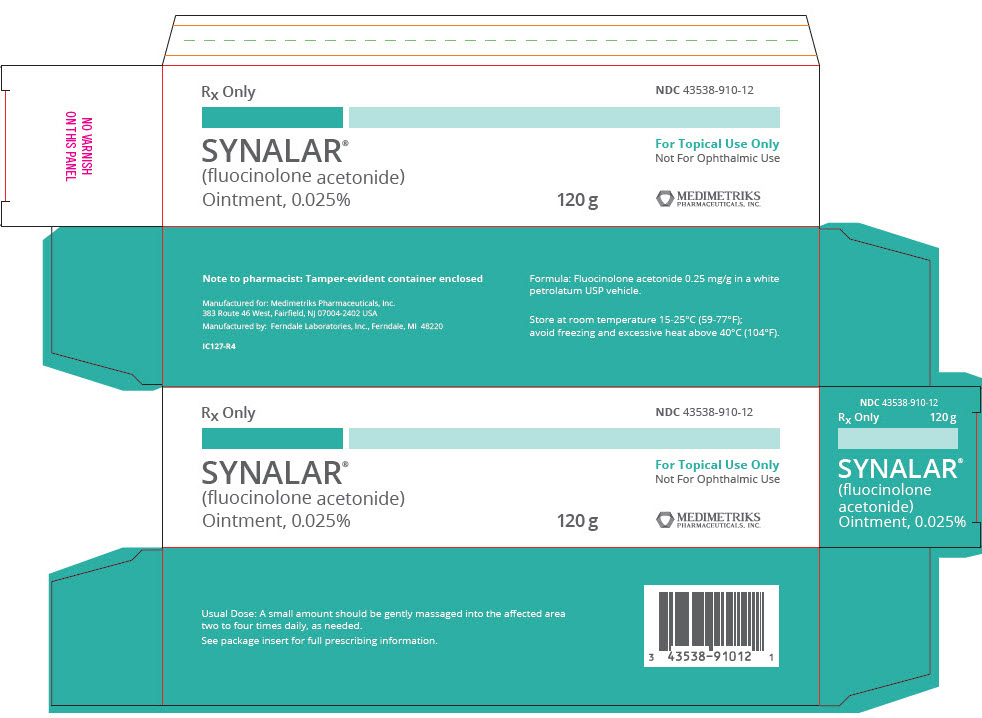 DRUG LABEL: Synalar
NDC: 43538-910 | Form: OINTMENT
Manufacturer: Medimetriks Pharmaceuticals, Inc.
Category: prescription | Type: HUMAN PRESCRIPTION DRUG LABEL
Date: 20231129

ACTIVE INGREDIENTS: fluocinolone acetonide 0.25 mg/1 g
INACTIVE INGREDIENTS: petrolatum

SYNALAR®
(fluocinolone acetonide)
Ointment, 0.025%

Rx Only

DESCRIPTION

SYNALAR® (fluocinolone acetonide) Ointment 0.025% is intended for topical administration. The active component is the corticosteroid fluocinolone acetonide, which has the chemical name pregna-1,4-diene-3,20-dione,6,9-difluoro-11,21-dihydroxy-16,17-[(1-methylethylidene)bis (oxy)]-,(6α,11β,16α)-. It has the following chemical structure:

SYNALAR® Ointment contains fluocinolone acetonide 0.25 mg/g in a white petrolatum USP vehicle.

CLINICAL PHARMACOLOGY

Topical corticosteroids share anti-inflammatory, anti-pruritic and vasoconstrictive actions.

The mechanism of anti-inflammatory activity of the topical corticosteroids is unclear. Various laboratory methods, including vasoconstrictor assays, are used to compare and predict potencies and/or clinical efficacies of the topical corticosteroids. There is some evidence to suggest that a recognizable correlation exists between vasoconstrictor potency and therapeutic efficacy in man.

Pharmacokinetics

The extent of percutaneous absorption of topical corticosteroids is determined by many factors including the vehicle, the integrity of the epidermal barrier, and the use of occlusive dressings.

Topical corticosteroids can be absorbed from normal intact skin. Inflammation and/or other disease processes in the skin increase percutaneous absorption. Occlusive dressings substantially increase the percutaneous absorption of topical corticosteroids. Thus, occlusive dressings may be a valuable therapeutic adjunct for treatment of resistant dermatoses (see DOSAGE AND ADMINISTRATION).

Once absorbed through the skin, topical corticosteroids are handled through pharmacokinetic pathways similar to systemically administered corticosteroids. Corticosteroids are bound to plasma proteins in varying degrees. Corticosteroids are metabolized primarily in the liver and are then excreted by the kidneys. Some of the topical corticosteroids and their metabolites are also excreted into the bile.

INDICATIONS AND USAGE

SYNALAR® Ointment is indicated for the relief of the inflammatory and pruritic manifestations of corticosteriod-responsive dermatoses.

CONTRAINDICATIONS

Topical corticosteroids are contraindicated in those patients with a history of hypersensitivity to any of the components of the preparation.

PRECAUTIONS

General

Systemic absorption of topical corticosteroids has produced reversible hypothalamic-pituitary-adrenal (HPA) axis suppression, manifestations of Cushing's syndrome, hyperglycemia, and glucosuria in some patients.

Conditions which augment systemic absorption include the application of the more potent steroids, use over large surface areas, prolonged use, and the addition of occlusive dressings.

Therefore, patients receiving a large dose of a potent topical steroid applied to a large surface area or under an occlusive dressing should be evaluated periodically for evidence of HPA axis suppression by using the urinary free cortisol and ACTH stimulation tests. If HPA axis suppression is noted, an attempt should be made to withdraw the drug, to reduce the frequency of application, or to substitute a less potent steroid.

Recovery of HPA axis function is generally prompt and complete upon discontinuation of the drug. Infrequently, signs and symptoms of steroid withdrawal may occur, requiring supplemental systemic corticosteroids.

Children may absorb proportionally larger amounts of topical corticosteroids and thus be more susceptible to systemic toxicity (see PRECAUTIONS—Pediatric Use).

If irritation develops, topical corticosteroids should be discontinued and appropriate therapy instituted.

As with any topical corticosteroid product, prolonged use may produce atrophy of the skin and subcutaneous tissues. When used on intertriginous or flexor areas, or on the face, this may occur even with short-term use.

In the presence of dermatological infections, the use of an appropriate antifungal or antibacterial agent should be instituted. If a favorable response does not occur promptly, the corticosteroid should be discontinued until the infection has been adequately controlled.

Information for the Patient

Patients using topical corticosteroids should receive the following information and instructions:

1. This medication is to be used as directed by the physician. It is for external use only. Avoid contact with the eyes.
2. Patients should be advised not to use this medication for any disorder other than that for which it was prescribed.
3. The treated skin area should not be bandaged or otherwise covered or wrapped as to be occlusive unless directed by the physician.
4. Patients should report any signs of local adverse reactions, especially under occlusive dressing.
5. Parents of pediatric patients should be advised not to use tight-fitting diapers or plastic pants on a child being treated in the diaper area, as these garments may constitute occlusive dressings.

Laboratory Tests

The following tests may be helpful in evaluating the HPA axis suppression:

Urinary free cortisol test
ACTH stimulation test

Carcinogenesis, Mutagenesis, and Impairment of Fertility

Long-term animal studies have not been performed to evaluate the carcinogenic potential or the effect on fertility of topical corticosteroids.

Studies to determine mutagenicity with prednisolone and hydrocortisone have revealed negative results.

Pregnancy

Corticosteroids are generally teratogenic in laboratory animals when administered systemically at relatively low dosage levels. The more potent corticosteroids have been shown to be teratogenic after dermal application in laboratory animals. There are no adequate and well-controlled studies in pregnant women on teratogenic effects from topically applied corticosteroids. Therefore, topical corticosteroids should be used during pregnancy only if the potential benefit justifies the potential risk to the fetus. Drugs of this class should not be used extensively on pregnant patients, in large amounts, or for prolonged periods of time.

Nursing Mothers

It is not known whether topical administration of corticosteroids could result in sufficient systemic absorption to produce detectable quantities in breast milk. Systemically administered corticosteroids are secreted into breast milk in quantities not likely to have a deleterious effect on the infant. Nevertheless, caution should be exercised when topical corticosteroids are administered to a nursing woman.

Pediatric Use

Pediatric patients may demonstrate greater susceptibility to topical corticosteroid-induced hypothalmic-pituitary-adrenal (HPA) axis suppression and Cushing's syndrome than mature patients because of a larger skin surface area to body weight ratio.

HPA axis suppression, Cushing's syndrome, and intracranial hypertension have been reported in children receiving topical corticosteroids. Manifestations of adrenal suppression in children include linear growth retardation, delayed weight gain, low plasma cortisol levels, and absence of response to ACTH stimulation. Manifestations of intracranial hypertension include bulging fontanelles, headaches, and bilateral papilledema.

Administration of topical corticosteroids to children should be limited to the least amount compatible with an effective therapeutic regimen. Chronic corticosteroid therapy may interfere with the growth and development of children.

ADVERSE REACTIONS

The following local adverse reactions are reported infrequently with topical corticosteroids, but may occur more frequently with the use of occlusive dressings. These reactions are listed in an approximate decreasing order of occurrence:

Burning | Hypertrichosis | Maceration of the skin
Itching | Acneiform eruptions | Secondary infection
Irritation | Hypopigmentation | Skin atrophy
Dryness | Perioral dermatitis | Striae
Folliculitis | Allergic contact dermatitis | Miliaria

OVERDOSAGE

Topically applied corticosteroids can be absorbed in sufficient amounts to produce systemic effects (see PRECAUTIONS).

DOSAGE AND ADMINISTRATION

SYNALAR® Ointment is generally applied to the affected area as a thin film from two to four times daily depending on the severity of the condition. In hairy sites, the hair should be parted to allow direct contact with the lesion.

Occlusive dressing may be used for the management of psoriasis or recalcitrant conditions. Some plastic films may be flammable and due care should be exercised in their use. Similarly, caution should be employed when such films are used on children or left in their proximity, to avoid the possibility of accidental suffocation.

If an infection develops, the use of the occlusive dressings should be discontinued and appropriate antimicrobial therapy instituted.

HOW SUPPLIED

SYNALAR® (fluocinolone acetonide) Ointment, 0.025% is supplied in

120 g Tube – NDC 43538-910-12

STORAGE

Store at room temperature 15-25°C (59-77°F); avoid freezing and excessive heat above 40°C (104°F).

To report SUSPECTED ADVERSE REACTIONS, contact Medimetriks Pharmaceuticals, Inc. at 1-973-882-7512 or FDA at 1-800-FDA-1088 or www.fda/gov/medwatch.

Manufactured for:

MEDIMETRIKS
PHARMACEUTICALS, INC.

383 Route 46 West, Fairfield, NJ 07004-2402 USA
www.medimetriks.com

Manufactured by: Ferndale Laboratories, Inc., Ferndale, MI 48220

IP029-R3
Rev. 10/2022

PRINCIPAL DISPLAY PANEL - 120 g Tube Carton

Rx Only

NDC 43538-910-12

SYNALAR®
(fluocinolone acetonide)
Ointment, 0.025%

For Topical Use Only
Not For Ophthalmic Use

120 g

MEDIMETRIKS
PHARMACEUTICALS, INC.